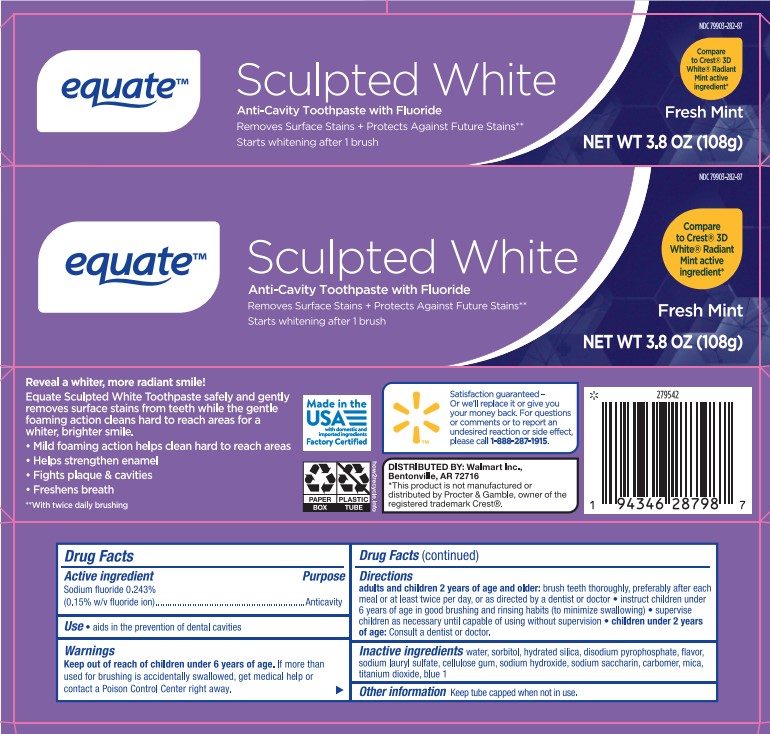 DRUG LABEL: Equate Sculpted White TP
NDC: 79903-282 | Form: PASTE, DENTIFRICE
Manufacturer: Walmart
Category: otc | Type: HUMAN OTC DRUG LABEL
Date: 20251113

ACTIVE INGREDIENTS: SODIUM FLUORIDE 0.15 g/100 g
INACTIVE INGREDIENTS: SORBITOL; SODIUM ACID PYROPHOSPHATE; CARBOXYMETHYLCELLULOSE SODIUM; CARBOXYPOLYMETHYLENE; FD&C BLUE NO. 1; MICA; TITANIUM DIOXIDE; WATER; HYDRATED SILICA; SACCHARIN SODIUM; SODIUM HYDROXIDE; SODIUM LAURYL SULFATE

5820079 Walmart Equate Schulpted White (80-15271)

ACTIVE INGREDIENT

Sodium fluoride 0.243% (0.15% w/v fluoride ion)

INACTIVE INGREDIENT

water, sorbitol, hydrated silica, disodium pyrophosphate, flavor, sodium lauryl sulfate, cellulose gum, sodium hydroxide, sodium saccharin, carbomer, mica, titanium dioxide, blue 1

PURPOSE

Anticavity

INDICATIONS AND USAGE

aids in the prevention of dental cavities

Keep out of reach of children under 6 years of age. If more than used for brushing is accidentally swallowed, get medical help or contact a Poison Control Center right away.

Keep out of reach of children under 6 years of age. If more than used for brushing is accidentally swallowed, get medical help or contact a Poison Control Center right away.

DOSAGE AND ADMINISTRATION

adults and children 2 years of age and older: brush teeth thoroughly, preferably after each meal or at least twice per day, or as directed by a dentist or doctor • instruct children under 6 years of age in good brushing habits (to minimize swallowing) • supervise children as necessary until capable of using without supervision • children under 2 years of age: Consult a dentist or doctor